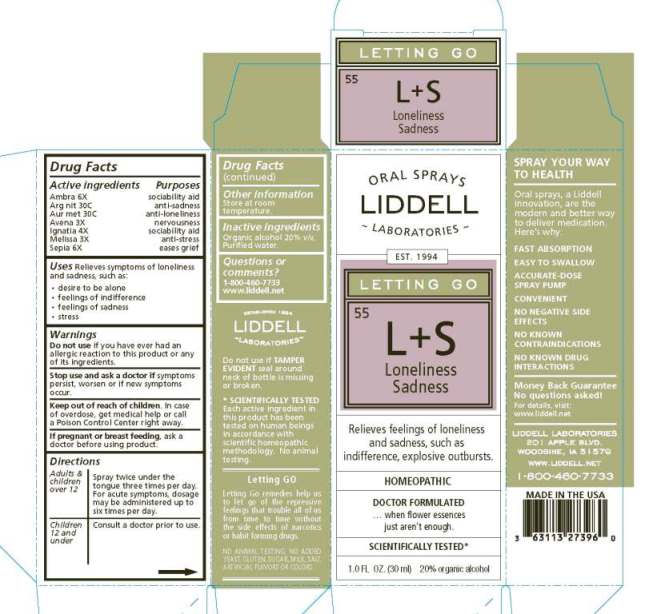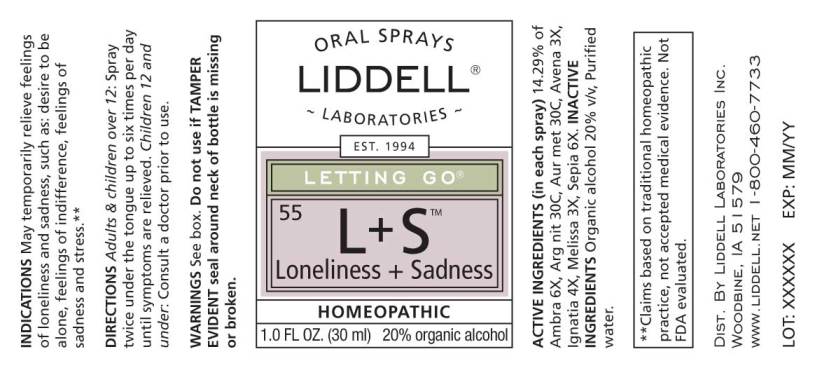 DRUG LABEL: Loneliness and Sadness
NDC: 50845-0050 | Form: SPRAY
Manufacturer: Liddell Laboratories
Category: homeopathic | Type: HUMAN OTC DRUG LABEL
Date: 20240701

ACTIVE INGREDIENTS: AMBERGRIS 6 [hp_X]/1 mL; SILVER NITRATE 30 [hp_C]/1 mL; GOLD 30 [hp_C]/1 mL; AVENA SATIVA FLOWERING TOP 3 [hp_X]/1 mL; STRYCHNOS IGNATII SEED 4 [hp_X]/1 mL; MELISSA OFFICINALIS WHOLE 3 [hp_X]/1 mL; SEPIA OFFICINALIS JUICE 6 [hp_X]/1 mL
INACTIVE INGREDIENTS: WATER; ALCOHOL

DRUG FACTS:

ACTIVE INGREDIENTS:

(in each spray): 14.29% of Ambra grisea 6X, Argentum nitricum 30C, Aurum metallicum 30C, Avena sativa 3X, Ignatia amara 4X, Melissa officinalis 3X, Sepia 6X.

USES:

Relieves symptoms of loneliness and sadness, such as:

•desire to be alone

•feelings of indifference

•feelings of sadness

•stress

**Claims based on traditional homeopathic practice, not accepted medical evidence. Not FDA evaluated.

WARNINGS:

Do not use if you have ever had an allergic reaction to this product or any of its ingredients.

Stop use and ask a doctor if symptoms persist, worsen or if new symptoms occur.

Keep out of reach of children. In case of overdose, get medical help or call a Poison Control Center right away.

If pregnant or breast feeding, ask a doctor before using product.

Do not use if TAMPER EVIDENT seal around neck of bottle is missing or broken.

Other information: Store at room temperature

DIRECTIONS:

Adults and children over 12: Spray twice under the tongue three times per day. For acute symptoms, dosage may be administered up to six times per day.

Children 12 and under: Consult a doctor prior to use.

KEEP OUT OF REACH OF CHILDREN:

Organic alcohol 20% v/v, Purified water.

INACTIVE INGREDIENTS:

Organic alcohol 20% v/v, Purified water.

INDICATIONS:

Relieves symptoms of loneliness and sadness, such as:

•desire to be alone

•feelings of indifference

•feelings of sadness

•stress

**Claims based on traditional homeopathic practice, not accepted medical evidence. Not FDA evaluated.

QUESTIONS:

LIDDELL LABORATORIES

201 APPLE BLVD.

WOODBINE, IA 51579

1-800-460-7733

WWW.LIDDELL.NET

PACKAGE LABEL DISPLAY:

ORAL SPRAYS
LIDDELL
LABORATORIES
EST 1994
LETTING GO
^55 L+S
Loneliness
Sadness
Relieves feelings of loneliness
and sadness, such as
indifference, explosive outbursts.
HOMEOPATHIC
DOCTOR FORMULATED
...when flower essences just aren't enough.
SCIENTIFICALLY TESTED
1.0 FL. OZ. (30 ml)